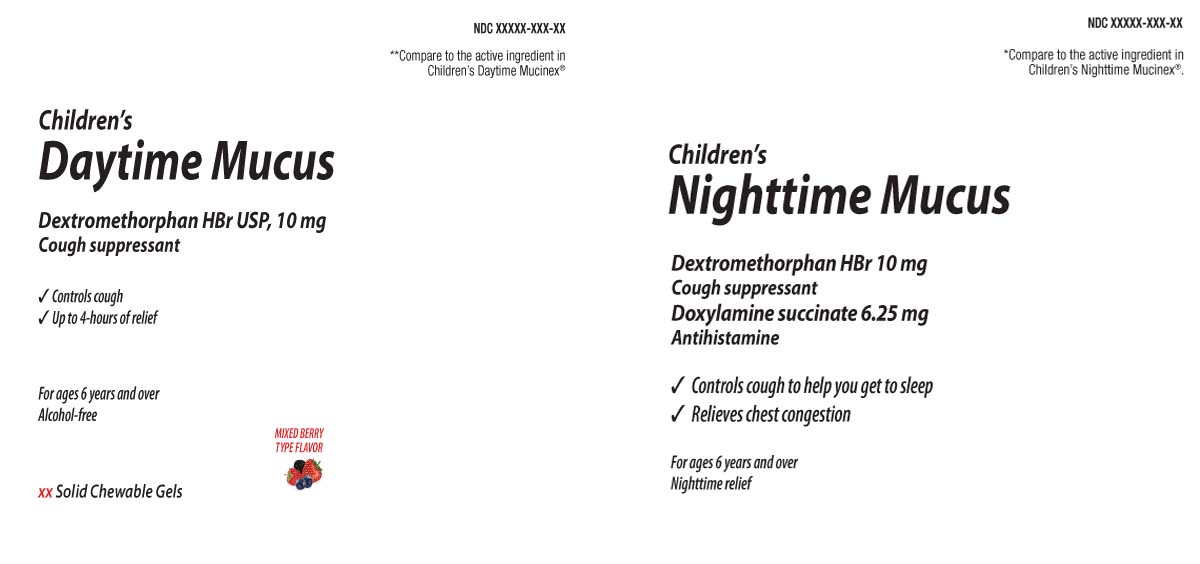 DRUG LABEL: Daytime Nighttime Chewable
NDC: 0363-9393 | Form: KIT | Route: ORAL
Manufacturer: Walgreens
Category: otc | Type: HUMAN OTC DRUG LABEL
Date: 20260213

ACTIVE INGREDIENTS: DEXTROMETHORPHAN HYDROBROMIDE 10 mg/1 1; DEXTROMETHORPHAN HYDROBROMIDE 10 mg/1 1; DOXYLAMINE SUCCINATE 6.25 mg/1 1
INACTIVE INGREDIENTS: ANHYDROUS CITRIC ACID; FD&C BLUE NO. 1; WATER; D&C RED NO. 33; MALIC ACID; SUCROSE; SORBITOL; GLYCERIN; SUCRALOSE; GLYCYRRHIZIN; CORN SYRUP; MALTODEXTRIN; MEDIUM-CHAIN TRIGLYCERIDES; PECTIN; PROPYLENE GLYCOL; TRISODIUM CITRATE DIHYDRATE; ALCOHOL; AMMONIUM GLYCYRRHIZATE; ANHYDROUS CITRIC ACID; FD&C RED NO. 40; FD&C BLUE NO. 1; CORN SYRUP; WATER; ALCOHOL; AMMONIUM GLYCYRRHIZATE; SUCRALOSE; GLYCERIN; SUCROSE; GLYCYRRHIZIN; MALIC ACID; MALTODEXTRIN; PECTIN; PROPYLENE GLYCOL; TRISODIUM CITRATE DIHYDRATE

Drug Facts

Active ingredient (in each chewable gel) Daytime

Dextromethorphan HBr 10 mg

Active ingredients for (in each chewable gel) NIGHTTIME

Dextromethorphan HBr 10 mg

Doxylamine Succinate 6.25 mg

Purposes for Day Time

Cough suppressant

Purpose for Night Time

Cough suppressant

Antihistamine

Uses

DAYTIME

- temporarily relieves cough due to minor throat and bronchial irritation

NIGHTTIME

- temporarily relieves cough due to minor throat and bronchial irritation as may occur with a cold
- controls cough to help you get to sleep
- temporarily relieves these symptoms due to hay fever or other upper respiratory allergies:
  - runny nose
  - itching of the nose or throat
  - sneezing
  - itchy, watery eyes

Warnings

Do not use

DAYTIME

- if you are now taking a prescription monoamine oxidase inhibitor (MAOI) (certain drugs for depression, psychiatric or emotional conditions, or Parkinson's disease), or for 2 weeks after stopping the MAOI drug. If you do not know if your prescription drug contains an MAOI, ask a doctor or pharmacist before taking this product.

NIGHTTIME

- to make a child sleepy
- if you are now taking a prescription monoamine oxidase inhibitor (MAOI) (certain drugs for depression, psychiatric or emotional conditions, or Parkinson’s disease), or for 2 weeks after stopping the MAOI drug. If you do not know if your prescription drug contains an MAOI, ask a doctor or pharmacist before taking this product

Ask a doctor before use if you have

DAYTIME

- cough that occurs with too much phlegm (mucus)
- persistent or chronic cough such as occurs with asthma

NIGHTTIME

- glaucoma
- cough that occurs with too much phlegm (mucus)
- a breathing problem or chronic cough that lasts or as occurs with smoking, asthma, chronic bronchitis, or emphysema
- trouble urinating due to enlarged prostate gland

Ask a doctor or pharmacist before use if you are

NIGHTTIME

taking sedatives or tranquilizers

When using this product

DAYTIME

do not use more than directed.

NIGHTTIME

- do not exceed recommended dosage
- excitability may occur, especially in children
- marked drowsiness may occur
- avoid alcoholic drinks
- be careful when driving a motor vehicle or operating machinery
- alcohol, sedatives and tranquilizers may increase drowsiness

Stop use and ask a doctor if

DAYTIME / NIGHTTIME

cough lasts more than 7 days, comes back, or occurs with fever, or headache that lasts. These could be signs of a serious condition.

If pregnant or breast-feeding,

DAYTIME NIGHTTIME

ask a health professional before use.

Keep out of reach of children.

DAYTIME / NIGHTTIME

In case of overdose, get medical help or contact a Poison Control Center(1-800-222-1222) right away.

Directions

DAYTIME / NIGHTTIME

- take every 4 hours or as directed by a doctor
- chew thoroughly before swallowing
- adults and children 12 years of age and over: 2 chewable gels every 4 hours, not to exceed 12 chewable gels in any 24-hour period
- children 6 years of age and over: 1 chewable gel every 4 hours, not to exceed 6 chewable gels in any 24-hour period
- children under 6 years of age: do not use

Other information

DAYTIME

- each chewable gel contains: sodium 8 mg
- store between 20-25ºC (68-77º). Do not refrigerate

NIGHTTIME

- each chewable gel contains sodium 6 mg
- store between 20-25ºC (68-77ºF). Do not refrigerate

Inactive ingredient

DAYTIME

alcohol, ammonium glycyrrhizate, citric acid anhydrous, corn syrup, FD&C Blue No. 1, FD&C red # 40, flavors, glycerin, glycyrrhizin, malic acid, maltodextrin, medium-chain triglycerides, pectin, propylene glycol, purified water, sorbitol solution, sucralose, sucrose, trisodium citrate dihydrate

NIGHTTIME

alcohol, ammonium glycyrrhizate, citric acid anhydrous, corn syrup, FD&C blue #1, FD&C Red #40, flavors, glycerin, glycyrrhizin, malic acid, maltodextrin, pectin, propylene glycol, purified water, sucralose, sucrose, trisodium citrate dihydrate

Questions or comments?

Call

Principal Display Panel

**Compare to the active ingredient in Mucinex® Children's Mighty Chews Cough Daytime

Children's

DayTime Mucus

Dextromethorphan HBr USP, 10 mg

Cough Suppressant

- Controls cough
- Up to 4-hours of relief

For ages 6 years and over

Alcohol Free

Solid Chewable Gels

MIXED BERRY FLAVOR

NightTime

*Compare to the active ingredient in Mucinex® Children's Mighty Chews Cough Nighttime

Children's

Nighttime Mucus

Dextromethorphan HBr 10 mg

Cough suppressant

Doxylamine Succinate

Antihistamine

- Controls cough to help you get to sleep
- Relieves chest congestion

For ages 6 years and over

Nighttime relief

Solid Chewable Gels

MIXED BERRY FLAVOR

**This product is not manufactured by RB Health (US) LLC, distributor of Mucinex® Children's Mighty Chews Cough Nighttime

TAMPER EVIDENT: DO NOT USE IF PRINTED SAFETY SEAL IS BROKEN OR MISSING.

DISTRIBUTED BY WALGREENS

Product Label

WALGREENS Daytime Nighttime Chewable Gels Mixed Berry Flavor